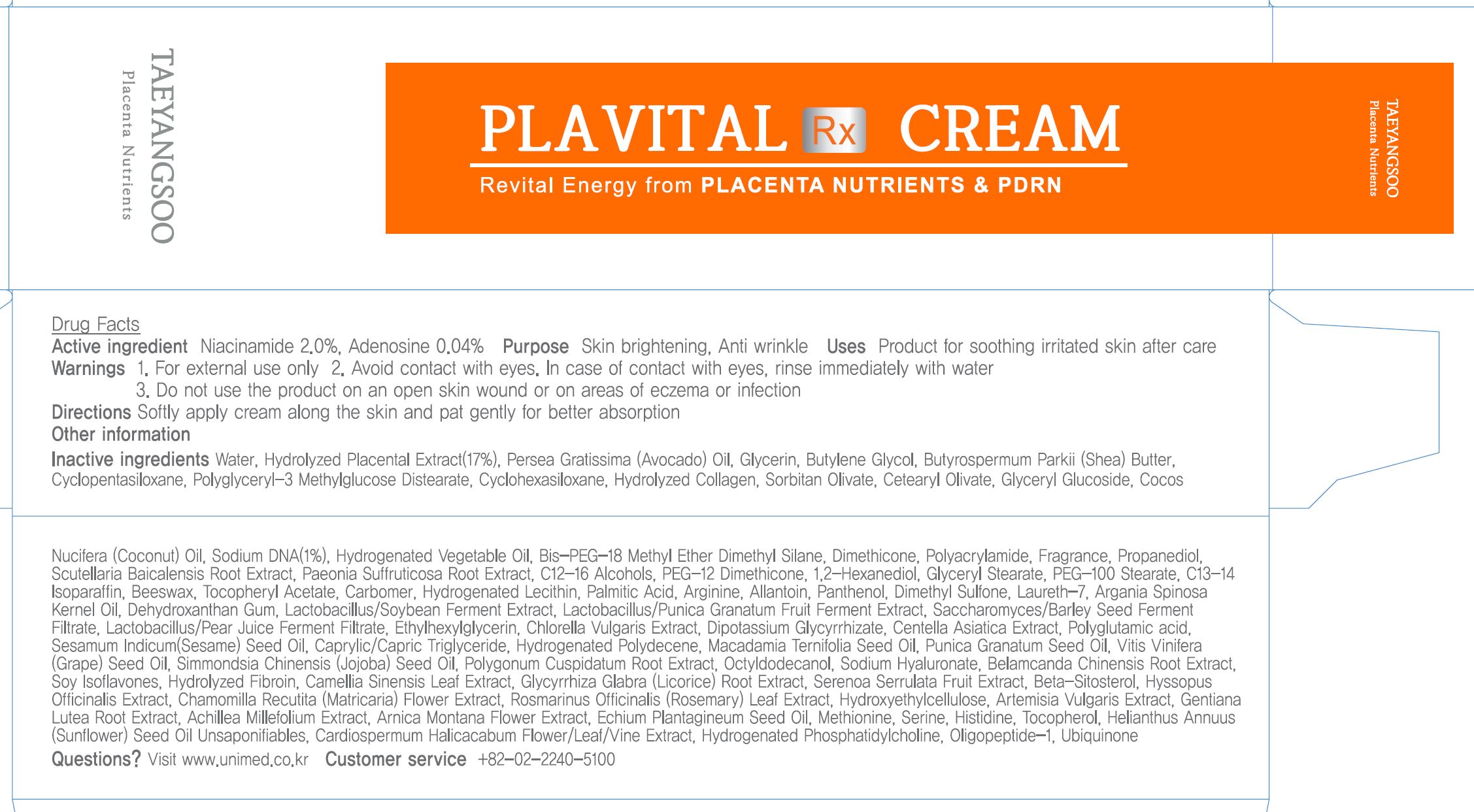 DRUG LABEL: TAEYANGSOO Plavital RxCream
NDC: 73669-004 | Form: CREAM
Manufacturer: Unimed Pharmaceuticals, Inc.
Category: otc | Type: HUMAN OTC DRUG LABEL
Date: 20200927

ACTIVE INGREDIENTS: NIACINAMIDE 2 g/100 g; ADENOSINE 0.04 g/100 g
INACTIVE INGREDIENTS: WATER

Drug Facts

ACTIVE INGREDIENT

adenosine, niacinamide

INACTIVE INGREDIENT

Butyrospermum Parkii (Shea) Butter
Glycerin
Polyglutamic acid
Methionine
Serine
Histidine
Butylene Glycol
Hydroxyethylcellulose
1,2-Hexanediol
Water
Cetearyl Olivate
Sorbitan Olivate
Scutellaria Baicalensis Root Extract
Paeonia Suffruticosa Root Extract
Glycerin
Butylene Glycol
Water
Polyacrylamide
C13-14 Isoparaffin
Laureth-7
Water
Glyceryl Glucoside
Glycerin
Water
Glycerin
Water
Chlorella Vulgaris Extract
Polyglyceryl-3 Methylglucose Distearate
Water
Propanediol
Glycerin
Lactobacillus/Soybean Ferment Extract
Lactobacillus/Punica Granatum Fruit Ferment Extract
Saccharomyces/Barley Seed Ferment Filtrate
Lactobacillus/Pear Juice Ferment Filtrate
Hydrolyzed Collagen
Cocos Nucifera (Coconut) Oil
Sodium DNA
Hydrogenated Vegetable Oil
Bis-PEG-18 Methyl Ether Dimethyl Silane
Butylene Glycol
Soy Isoflavones
C12-16 Alcohols
Hydrogenated Lecithin
Palmitic Acid
Dimethicone
Water
Butylene Glycol
Artemisia Vulgaris Extract
Gentiana Lutea Root Extract
Achillea Millefolium Extract
Arnica Montana Flower Extract
1,2-Hexanediol
Water
Butylene Glycol
Belamcanda Chinensis Root Extract
1,2-Hexanediol
Glyceryl Stearate
PEG-100 Stearate
Fragrance
Butylene Glycol
Water
Centella Asiatica Extract
Polygonum Cuspidatum Root Extract
Scutellaria Baicalensis Root Extract
Camellia Sinensis Leaf Extract
Glycyrrhiza Glabra (Licorice) Root Extract
Chamomilla Recutita (Matricaria) Flower Extract
Rosmarinus Officinalis (Rosemary) Leaf Extract
PEG-12 Dimethicone
Sorbitan Olivate
Water
Butylene Glycol
Hyssopus Officinalis Extract
1,2-Hexanediol
Beeswax
Tocopheryl Acetate
Carbomer
Arginine
Macadamia Ternifolia Seed Oil
Allantoin
Dimethyl Sulfone
Oligopeptide-1
1,2-Hexanediol
Water
Panthenol
Serenoa Serrulata Fruit Extract
Sesamum Indicum (Sesame) Seed Oil
Argania Spinosa Kernel Oil
Beta-Sitosterol
Tocopherol
Dehydroxanthan Gum
Ethylhexylglycerin
Dipotassium Glycyrrhizate
Simmondsia Chinensis (Jojoba) Seed Oil
Hydrogenated Polydecene
Octyldodecanol
Echium Plantagineum Seed Oil
Helianthus Annuus (Sunflower) Seed Oil Unsaponifiables
Cardiospermum Halicacabum Flower/Leaf/Vine Extract
Tocopherol
Punica Granatum Seed Oil
Vitis Vinifera (Grape) Seed Oil
Caprylic/Capric Triglyceride
Hydrolyzed Fibroin
Sodium Hyaluronate
Water
Glycerin
Butylene Glycol
1,2-Hexanediol
Hydrogenated Phosphatidylcholine
Caprylic/Capric Triglyceride
Ubiquinone

PURPOSE

anti-wrinkle, whitening

keep out of reach of the children

INDICATIONS AND USAGE

apply proper amount to the skin

WARNINGS

For external use only
When using this product

■ if the following symptoms occurs after use, stop use and consult with a skin specialist

red specks, swelling, itching

■ don’t use on the part where there is injury, eczema, or dermatitis

Keep out of reach of children

■ if swallowed, get medical help or contact a person control center immediately

DOSAGE AND ADMINISTRATION

external use only